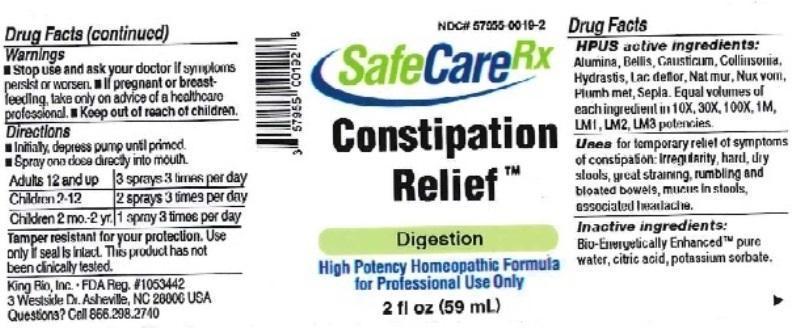 DRUG LABEL: Constipation Relief
NDC: 57955-0019 | Form: LIQUID
Manufacturer: King Bio Inc.
Category: homeopathic | Type: HUMAN OTC DRUG LABEL
Date: 20160627

ACTIVE INGREDIENTS: ALUMINUM OXIDE 10 [hp_X]/59 mL; BELLIS PERENNIS 10 [hp_X]/59 mL; CAUSTICUM 10 [hp_X]/59 mL; COLLINSONIA CANADENSIS ROOT 10 [hp_X]/59 mL; GOLDENSEAL 10 [hp_X]/59 mL; SKIM MILK 10 [hp_X]/59 mL; SODIUM CHLORIDE 10 [hp_X]/59 mL; STRYCHNOS NUX-VOMICA SEED 10 [hp_X]/59 mL; LEAD 10 [hp_X]/59 mL; SEPIA OFFICINALIS JUICE 10 [hp_X]/59 mL
INACTIVE INGREDIENTS: ANHYDROUS CITRIC ACID; POTASSIUM SORBATE; WATER

Constipation Relief™

ACTIVE INGREDIENT

Drug Facts__________________________________________________________________________________________________________

HPUS active ingredients: Alumina, Bellis perennis, Causticum, Collinsonia canadensis, Hydrastis canadensis, Lac defloratum, Natrum muriaticum, Nux vomica, Plumbum metallicum, Sepia. Equal volumes of each ingredient in 10X, 30X, 100X, 1M, LM1, LM2, LM3 potencies.

INDICATIONS AND USAGE

Uses for temporary relief of symptoms of constipation: irregularity, hard, dry stools, great straining, rumbling and bloated bowels, mucus in stools, associated headache.

Inactive Ingredients:

Bio-Energetically Enhanced™ pure water, citric acid and potassium sorbate.

Warnings

- Stop use and ask your doctor if symptoms persist or worsen.
- If pregnant or breast-feeding, take only on advice of a healthcare professional.

- Keep out of reach of children.

Directions

- Initially, depress pump until primed.
- Spray one dose directly into mouth.
- Adults 12 and up: 3 sprays 3 times per day.
- Children 2-12: 2 sprays 3 times per day.
- Children 2 mo.-2yr: 1 spray 3 times per day.

OTHER SAFETY INFORMATION

Tamper resistant for your protection. Use only if safety seal is intact. This product has not been clinically tested.

PURPOSE

Uses for temporary relief of symptoms of constipation:

- irregularity
- hard, dry stools
- great straining
- rumbling and bloated bowels
- mucus in stools
- associated headache